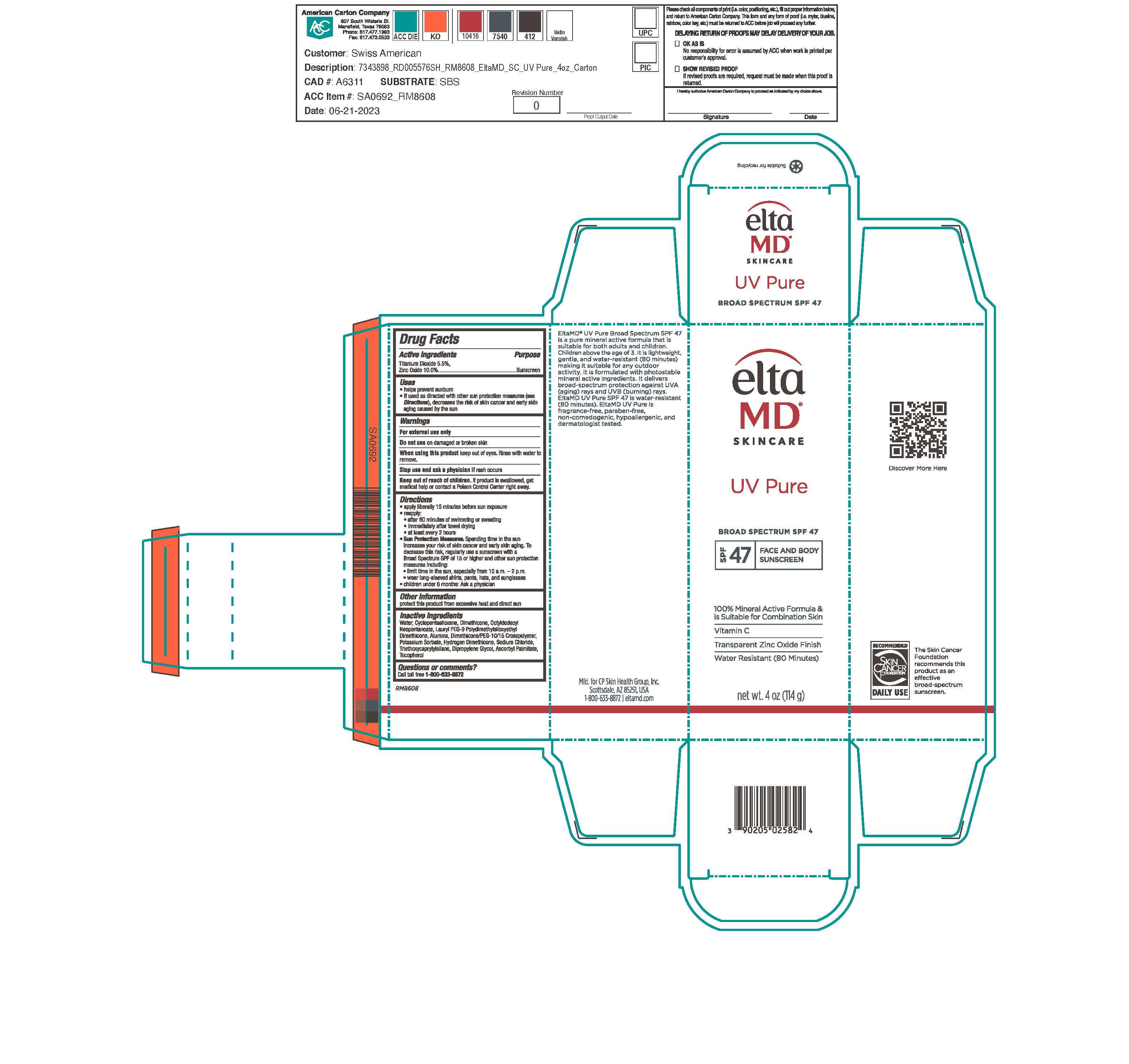 DRUG LABEL: EltaMD UV Pure SPF47
NDC: 72043-2582 | Form: CREAM
Manufacturer: CP Skin Health Group, Inc.
Category: otc | Type: HUMAN OTC DRUG LABEL
Date: 20240327

ACTIVE INGREDIENTS: ZINC OXIDE 100 g/1000 g; TITANIUM DIOXIDE 55 g/1000 g
INACTIVE INGREDIENTS: WATER; POTASSIUM SORBATE; SODIUM CHLORIDE; CITRIC ACID MONOHYDRATE; DIMETHICONE; CYCLOMETHICONE 5; OCTYLDODECYL NEOPENTANOATE; ASCORBYL PALMITATE; LAURYL PEG-9 POLYDIMETHYLSILOXYETHYL DIMETHICONE; TRIETHOXYCAPRYLYLSILANE; HYDROGEN DIMETHICONE (13 CST); ALUMINUM OXIDE

EltaMD UV Pure SPF47

Warnings

For external use only Do not use on damaged or broken skin When using this product keep out of eyes. Rinse with water to remove. Stop use and ask a physician if rash occurs Keep out of reach of children. If product is swallowed, get medical help or contact a Poison Control Center right away.

Active Ingredients

Zinc Oxide 10.0% Sunscreen

Titanium Dioxide 5.5% Sunscreen

Uses

helps prevents sunburn if used as directed with other sun protection measures (see Directions), decreases the risk of skin cancer and early skin aging caused by the sun

Uses

helps prevents sunburn if used as directed with other sun protection measures (see Directions), decreases the risk of skin cancer and early skin aging caused by the sun

Directions

Apply liberally 15 minutes before sun exposure Reapply after 80 minutes of swimming or sweating immediately after towel drying at least every 2 hours Sun Protection Measures. Spending time int he sun increases your risk of skin cancer and early skin aging. To decrease this risk, egularly use a sunscreen with a broad-spectrum SPF of 15 or higher and other sun protection measures including: limit time in the sun, especially from 10 a.m. - 2 p.m. wear long-sleeve shirts, pants, hats and sunglasses Children under 6 months: Ask a physician.

Inactive Ingredients

Purified Water, Cyclopentasiloxane, Dimethicone, Octyldodecyl neopentanoate, laury PEG-9 Polydimethylsiloxyethyl Dimethicone, Dimethicone/PEG-10/15 Crosspolymer, Ascorbyl Palmitate, Tocopherol, Sodium Chloride, Triethoxycaprylylsilane, Alumina, Hydrogen Dimethicone, Potassium Sorbate, Citric Acid

KEEP OUT OF REACH OF CHILDREN